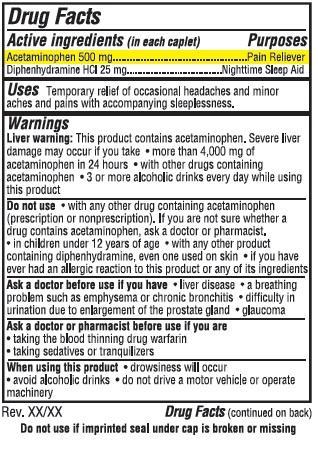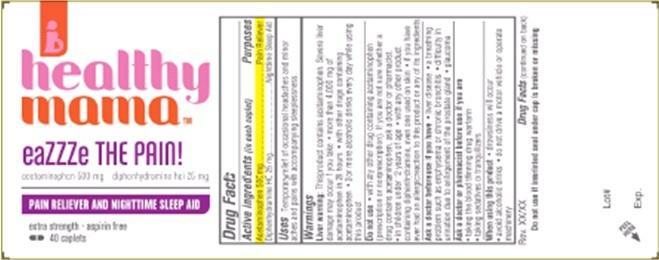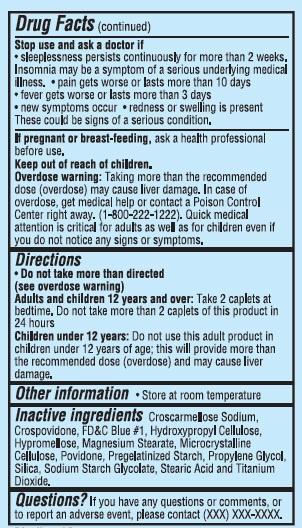 DRUG LABEL: healthy mama
NDC: 58154-104 | Form: TABLET, FILM COATED
Manufacturer: MATERNAL SCIENCE, LLC
Category: otc | Type: HUMAN OTC DRUG LABEL
Date: 20130429

ACTIVE INGREDIENTS: ACETAMINOPHEN 500 mg/1 1; DIPHENHYDRAMINE HYDROCHLORIDE 25 mg/1 1
INACTIVE INGREDIENTS: CROSCARMELLOSE SODIUM; CROSPOVIDONE; FD&C BLUE NO. 1; HYPROMELLOSES; MAGNESIUM STEARATE; CELLULOSE, MICROCRYSTALLINE; POVIDONES; PROPYLENE GLYCOL; SILICON DIOXIDE; STEARIC ACID; TITANIUM DIOXIDE

Drug Facts

Active ingredient (in each caplet)

Acetaminophen 500 mg

Diphenhydramine HCl 25mg

Purposes

Pain RelieverNighttime Sleep Aid

Uses

Temporary relief of occasional headaches and minor aches with pains with accompanying sleeplessness.

Warnings

Liver warning: This product contains acetaminophen. Severe Liver damage may occur if you take.

- more than 4,000 mg of acetaminophen in 24 hours
- with other drugs containing acetaminophen
- 3 or more alcoholic drinks everyday while using this product

When using this prodcut

- drowsiness will occur
- avoid alcoholic drinks
- do not drive a motor vehicle or operate machinery

Keep out of reach of children.

Do not use

- with any other drug containing acetaminophen(prescription or nonprescription). If you are not sure whether a drug contains acetaminophen, ask a doctor or pharmacist.
- In children under 12 years of age
- with any other product containing diphenhydramine, even one used on skin
- if you have ever had an allergic reaction to this product or any of its ingredients

Ask a doctor before use if you are

- liver disease
- a breathing problem such as emphysema or chronic bronchitis
- difficulty in urination due to enlargement of the prostate gland
- glaucoma

Ask a doctor or pharmacist before use if you are

- taking the blood thinning drug warfarin
- taking sedatives or tranquilizers

Stop use and ask a doctor if

- sleeplessness persists continuously for more than 2 weeks. Insomnia may be a symptom of a serious underlying medical illness.
- pain gets worse or lasts more than 10 days
- fever gets worse or lasts more than 3 days
- new symptoms occur
- redness or swelling is present. These could be signs of a serious condition.

PREGNANCY OR BREAST FEEDING

If pregnant or breast-feeding, ask a health professional before use.

Overdose warning

Taking more than the recommended dose(overdose) may cause liver damage. In case of overdose, get medical help or contact a Poison Control Center right away.(1-800-222-1222). Quick medical attention is critical for adults as well as for children even if you do not notice any signs or symptoms.

Directions

- Do not take more than directed (see overdose warning)

Adults and children 12 years and over: Take 2 caplets at bedtime. Do not take more than 2 caplets of this product in 24 hours

Children under 12 years: Do not use this adult product in children under 12 years of age: this will provide more than the

recommended dose(overdose) and may cause liver damage.

Other information

- Store at room temperature

Inactive ingredients

Povidone, Pregelatinized Starch, Sodium Starch Glycolate, Stearic Acid.

Questions?

If you have any questions or comments. or to report an adverse event, please contact (xxx) xxx-xxxx.

Principal Display Panel

healthy

mama

eaZZZe THE PAIN!

acetaminophen 500mg diphenhydramine HCl 25 mg

PAIN RELIEVER AND NIGHTTIME AID

extra strength aspirin free

40 caplets